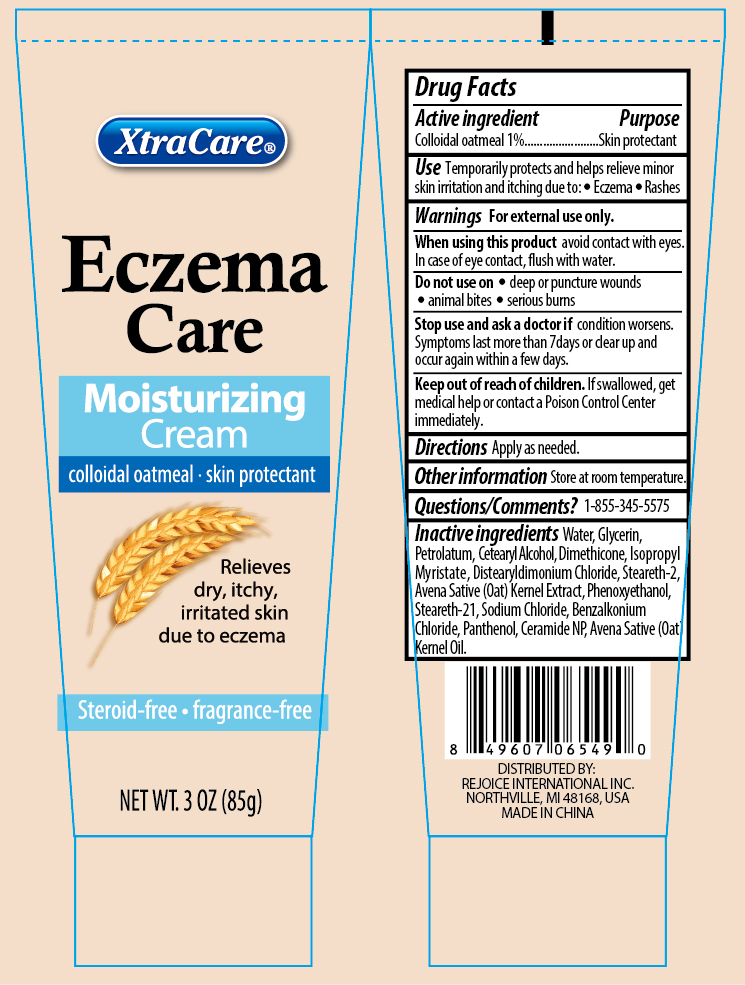 DRUG LABEL: Eczema Care Moisturizing
NDC: 58503-119 | Form: LOTION
Manufacturer: China Ningbo Shangge Technology Co., Ltd.
Category: otc | Type: HUMAN OTC DRUG LABEL
Date: 20190308

ACTIVE INGREDIENTS: OATMEAL 10 mg/1 mL
INACTIVE INGREDIENTS: WATER; GLYCERIN; DISTEARYLDIMONIUM CHLORIDE; PANTHENOL; PETROLATUM; ISOPROPYL MYRISTATE; CETYL ALCOHOL; DIMETHICONE; OAT KERNEL OIL; STEARETH-20; OAT; BENZALKONIUM CHLORIDE; CERAMIDE NP; SODIUM CHLORIDE; PHENOXYETHANOL; STEARETH-2; CETOSTEARYL ALCOHOL

Eczema Care Moisturizing Cream 3 oz.

Active ingredient

Colloidal Oatmeal 1%

Purpose

Skin protectant

Uses

- Temporarily protects and helps relieve minor skin itching and irritation due to:
- Eczema
- Rashes

Warnings

For external use only.

When using this product

- avoid contact with eyes. In case of eye contact, flush with water.

Stop using this product and ask a doctor if

- condition worsens, or if symptoms last more than 7 days, or if they clear up and occur again within a few days.

Keep out of reach of children.

- In case of accidental ingestion, get medical help or contact a Poison Control Center immediately.

Directions

Apply as needed

Other information

- store at room temperature.

Inactive ingredients

Water, Glycerin, Petrolatum, Cetearyl Alcohol, Dimethicone, Isopropyl Myristate, Distearyldimonium Chloride, Steareth-2, Avena Sativa (Oat) Kernel Extract, Phenoxyethanol, Steareth-21, Sodium Chloride, Benzalkonium Chloride, Panthenol, Ceramide NP, Avena Sativa (Oat) Kernel Oil